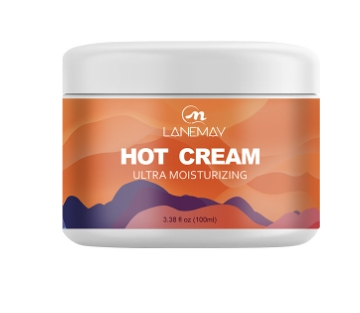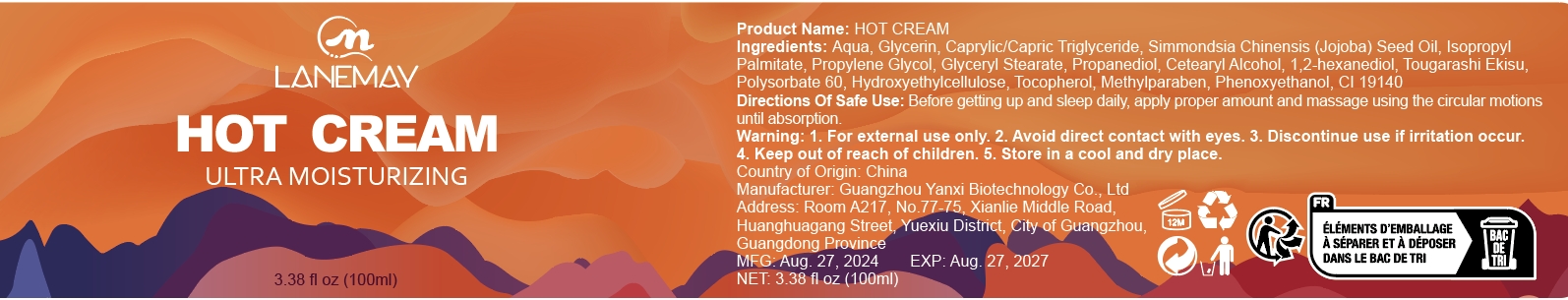 DRUG LABEL: hot cream
NDC: 84025-247 | Form: CREAM
Manufacturer: Guangzhou Yanxi Biotechnology Co., Ltd
Category: otc | Type: HUMAN OTC DRUG LABEL
Date: 20241104

ACTIVE INGREDIENTS: GLYCERIN 5 mg/100 mL; CAPRYLIC/CAPRIC TRIGLYCERIDE 3 mg/100 mL
INACTIVE INGREDIENTS: WATER

DOSAGE AND ADMINISTRATION

Before getting up and sleep daily, apply proper amount and massage using the circular motions until absorption.

WARNINGS

Keep out of children

INACTIVE INGREDIENT

Aqua

INDICATIONS AND USAGE

For daily skin care

Keep out of children

PURPOSE

Skin moisturizing